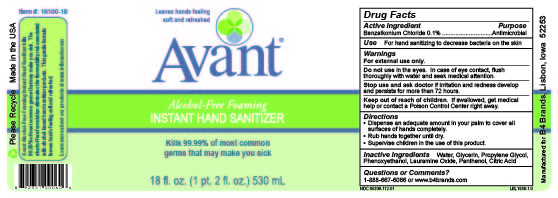 DRUG LABEL: Avant Alcohol-Free Instant Hand Sanitizer
NDC: 68306-112 | Form: SOLUTION
Manufacturer: B4 Ventures LLC
Category: otc | Type: HUMAN OTC DRUG LABEL
Date: 20240801

ACTIVE INGREDIENTS: BENZALKONIUM CHLORIDE 1 g/1000 mL
INACTIVE INGREDIENTS: CITRIC ACID MONOHYDRATE; WATER; PANTHENOL; GLYCERIN; PHENOXYETHANOL; PROPYLENE GLYCOL; LAURAMINE OXIDE

Avant Alcohol-Free Foaming Instant Hand Sanitizer

Active Ingredient

Benzalkonium Chloride 0.1%

Purpose

Antimicrobial

Use

For hand sanitizing to decrease bacteria on the skin

Warnings

For external use only.

Do not use in the eyes. In case of eye contact, flush thoroughly with water and seek medical attention.

Stop use and ask doctor if irritation and redness develop and persists for more than 72 hours.

Keep out of reach of children. If swallowed, get medical help or contact a Poison Control Center right away.

Directions

- Dispense an adequate amount in your palm to cover all surfaces of hands completely.
- Rub hands together until dry.
- Supervise children in the use of this product.

Inactive Ingredients

Water, Glycerin, Propylene Glycol, Phenoxyethanol, Lauramine Oxide, Panthenol, Citric Acid

Questions or Comments?

1-888-667-6066 or www.b4brands.com